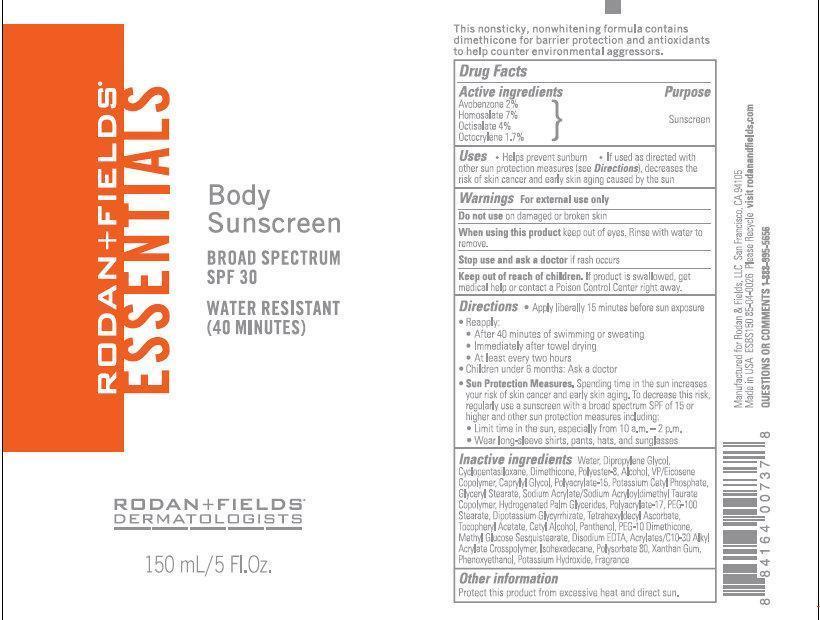 DRUG LABEL: RODAN - FIELDS ESSENTIALS Body Sunscreen BROAD SPECTRUM SPF 30
NDC: 14222-0001 | Form: CREAM
Manufacturer: Rodan & Fields
Category: otc | Type: HUMAN OTC DRUG LABEL
Date: 20250131

ACTIVE INGREDIENTS: AVOBENZONE 20 mg/1 mL; HOMOSALATE 70 mg/1 mL; OCTISALATE 40 mg/1 mL; OCTOCRYLENE 17 mg/1 mL
INACTIVE INGREDIENTS: ISOHEXADECANE; POLYSORBATE 80; XANTHAN GUM; PHENOXYETHANOL; POTASSIUM HYDROXIDE; WATER; DIPROPYLENE GLYCOL; CYCLOMETHICONE 5; DIMETHICONE; ALCOHOL; CAPRYLYL GLYCOL; POTASSIUM CETYL PHOSPHATE; GLYCERYL MONOSTEARATE; HYDROGENATED PALM GLYCERIDES; PEG-100 STEARATE; GLYCYRRHIZINATE DIPOTASSIUM; TETRAHEXYLDECYL ASCORBATE; .ALPHA.-TOCOPHEROL ACETATE; CETYL ALCOHOL; PANTHENOL; EDETATE DISODIUM

RODAN + FIELDS ESSENTIALS Body Sunscreen BROAD SPECTRUM SPF 30

Active ingredients

Avobenzone 2% Homosalate 7% Octisalate 4% Octocrylene 1.7%

Purpose

Sunscreen

Uses

- Helps prevent sunburn
- If used as directed with other sun protection measures (see), decreases the risk of skin cancer and early skin aging caused by the sun Directions

Warnings

For external use only

Do not use

on damaged or broken skin

When using this product

keep out of eyes. Rinse with water to remove.

Stop use and ask a doctor

if rash occurs

Keep out of reach of children.

If product is swallowed, get medical help or contact a Poison Control Center right away.

Directions

- Apply liberally 15 minutes before sun exposure
- Reapply:
- After 40 minutes of swimming or sweating
- Immediately after towel drying
- At least every two hours
- Children under 6 months: Ask a doctor
- Spending time in the sun increases your risk of skin cancer and early skin aging. To decrease this risk, regularly use a sunscreen with a broad spectrum SPF of 15 or higher and other sun protection measures including: Sun Protection Measures.
- Limit time in the sun, especially from 10 a.m. - 2 p.m.
- Wear long-sleeve shirts, pants, hats, and sunglasses

Inactive ingredients

Water, Dipropylene Glycol, Cyclopentasiloxane, Dimethicone, Polyester-8, Alcohol, VP/Eicosene Copolymer, Caprylyl Glycol, Polyacrylate-15, Potassium Cetyl Phosphate, Glyceryl Stearate, Sodium Acrylate/Sodium Acryloyldimethyl Taurate Copolymer, Hydrogenated Palm Glycerides, Polyacrylate-17, PEG-100 Stearate, Dipotassium Glycyrrhizate, Tetrahexyldecyl Ascorbate, Tocopheryl Acetate, Cetyl Alcohol, Panthenol, PEG-10 Dimethicone, Methyl Glucose Sesquistearate, Disodium EDTA, Acrylates/C10-30 Alkyl Acrylate Crosspolymer, Isohexadecane, Polysorbate 80, Xanthan Gum, Phenoxyethanol, Potassium Hydroxide, Fragrance.

Other information

Protect this product from excessive heat and direct sun.

RODAN - FIELDS ESSENTIALS

This non sticky, non whitening formula contains dimethicone for barrier protection and antioxidants to help counter environmental aggressors. Manufactured for Rodan and Fields, LLC San Francisco, CA 94105 Made in USA ESBS150 85-04-0026 Please Recycle
visit rodanandfields.com QUESTIONS OR COMMENTS 1-888-995-5656

PACKAGE LABEL

RODAN + FIELDS ESSENTIALS Body Sunscreen BROAD SPECTRUM SPF 30 WATER RESISTANT (40 MINUTES) RODAN + FIELDS DERMATOLOGISTS 150 mL/5 Fl.Oz.